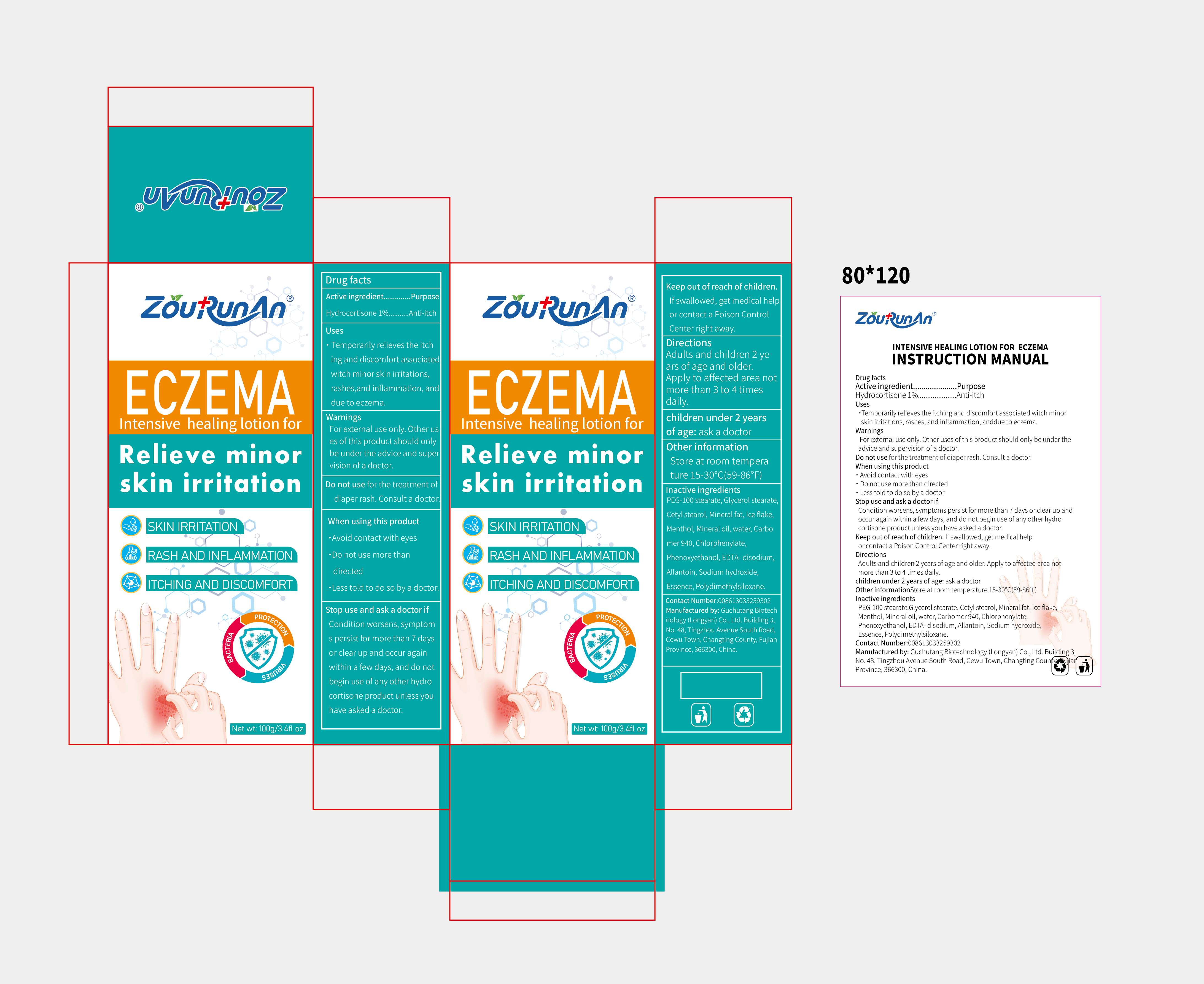 DRUG LABEL: zourunan Intensive healing lotion. for ECZEMA
NDC: 87083-002 | Form: CREAM
Manufacturer: Guchutang Biotechnology (Longyan) Co., Ltd
Category: otc | Type: HUMAN OTC DRUG LABEL
Date: 20251029

ACTIVE INGREDIENTS: HYDROCORTISONE 1 g/100 g
INACTIVE INGREDIENTS: MENTHOL, (+)-; CARBOMER 940; ALLANTOIN; PETROLATUM; EDETATE CALCIUM DISODIUM; GLYCERYL MONOSTEARATE; PEG-60 STEARATE; WATER; DIMETHICONE; MINERAL OIL; PHENOXYETHANOL; SODIUM HYDROXIDE; CETOSTEARYL ALCOHOL

87083-002 Update Change M017

Active Ingredient

Hydrocortisone 1%

Purpose

Anti-itch

Use

Temporarily relieves the itching and discomfort associated witch minor skin irritations, rashes,and inflammation,anddue to eczema.

Warnings

For external use only.Other uses of this product should only be under the advice and supervision of a doctor.

Do not use

for the treatment of diaper rash.Consult a doctor.

When Using

·Avoid contact with eyes
·Do not use more than directed
·Less told to do so by a doctor

Stop Use

Condition worsens, symptoms persist for more than 7 days or clear up and occur again within a few days, and do not begin use of any other hydrocortisone product unless you have asked a doctor.

Ask Doctor

do not begin use of any other hydrocortisone product unless you have asked a doctor.

Keep Out Of Reach Of Children

If swallowed, get medical help or contact a Poison Control Center right away.

Directions

Adults and children 2 years of age and older. Apply to affected area not more than 3 to 4 times daily.

Other information

Store at room temperature 15-30℃(59-86℉)

Inactive ingredients

PEG-100 stearate,Glycerol stearate, Cetyl stearol, Mineral fat, Ice flake,Menthol, Mineral oil, water, Carbomer 940, Chlorphenylate,
Phenoxyethanol, EDTA- disodium, Allantoin, Sodium hydroxide, Essence,Polydimethylsiloxane.